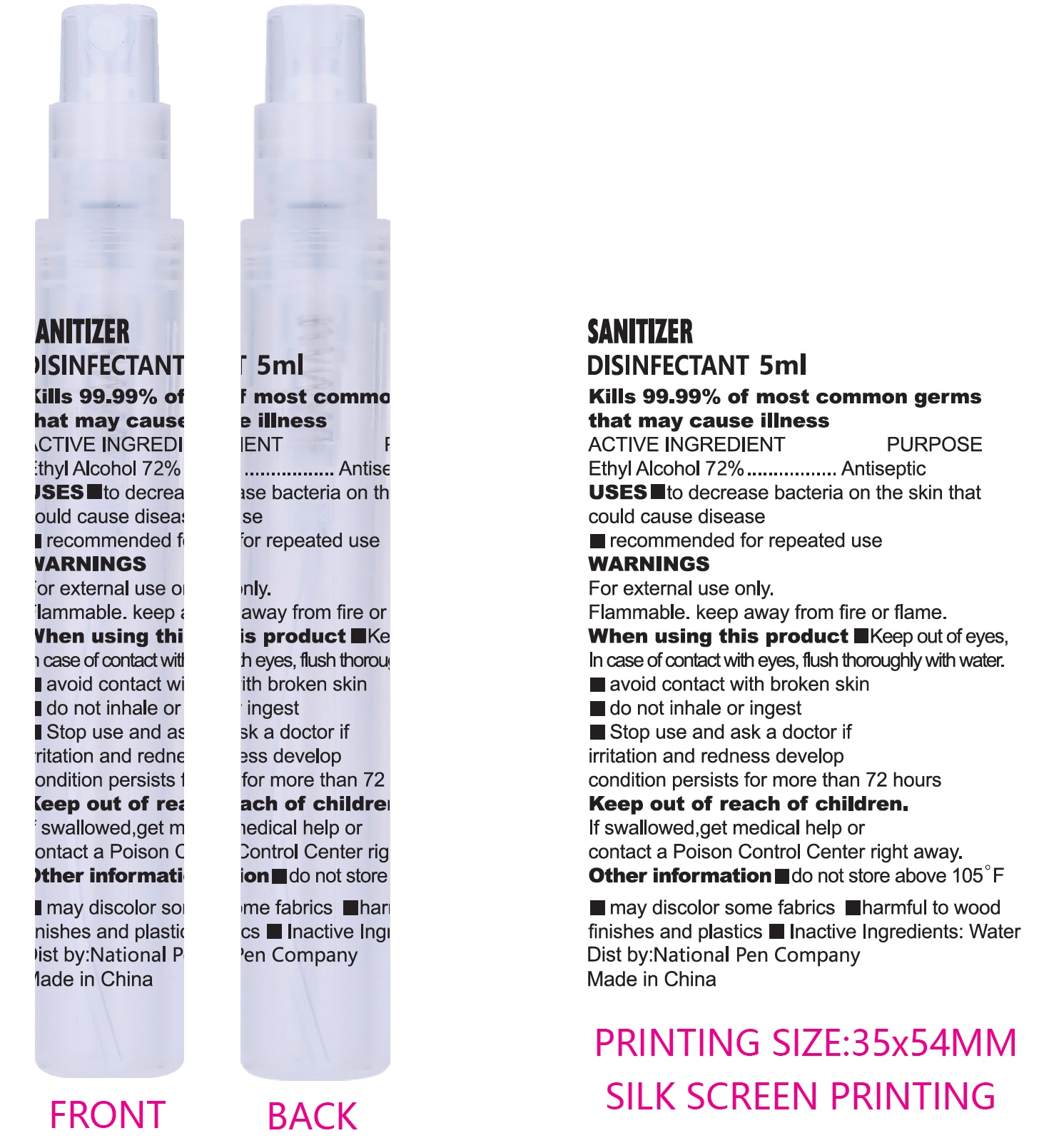 DRUG LABEL: Sanitizer disinfectant
NDC: 80575-004 | Form: SPRAY
Manufacturer: National Design LLC
Category: otc | Type: HUMAN OTC DRUG LABEL
Date: 20200929

ACTIVE INGREDIENTS: ALCOHOL 0.72 mL/1 mL
INACTIVE INGREDIENTS: WATER

Sanitizer disinfectant

ACTIVE INGREDIENT

Ethyl Alcohol 72%

PURPOSE

Antiseptic

USES

- to decrease bacteria on the skin that could cause disease
- recommended for repeated use

WARNINGS

For external use only.

Flammable. keep away from fire or flame.

When using this product

- Keep out of eyes, In case of contact with eyes, flush thoroughly with water.
- avoid contact with broken skin
- do not inhale or ingest

Stop use and ask a doctor if

irritation and redness develop condition persists for more than 72 hours

Keep out of reach of children.

If swallowed, get medical help or contact a Poison Control Center right away.

Other information

- do not store above 105°F
- may discolor some fabrics
- harmful to wood finishes and plastics

Inactive Ingredients:

Water